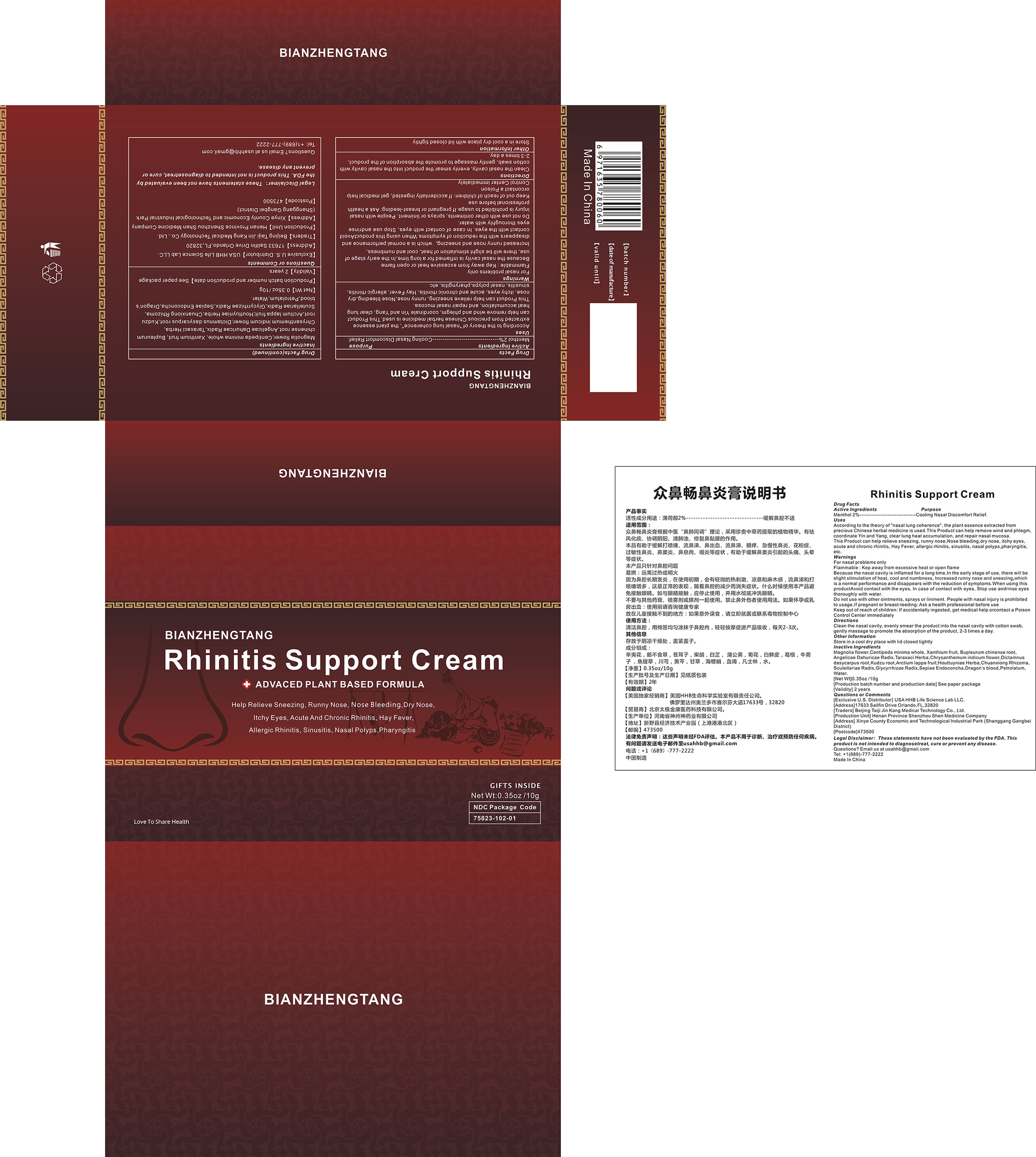 DRUG LABEL: Rhinitis Support Cream
NDC: 75823-102 | Form: CREAM
Manufacturer: Beijing Taiji Jin Kang Medical Technology Co., Ltd.
Category: otc | Type: HUMAN OTC DRUG LABEL
Date: 20200820

ACTIVE INGREDIENTS: MENTHOL 2 g/100 g
INACTIVE INGREDIENTS: PETROLATUM; MAGNOLIA SPRENGERI FLOWER BUD; CENTIPEDA MINIMA WHOLE; XANTHIUM SIBIRICUM FRUIT; BUPLEURUM CHINENSE ROOT; ANGELICA DAHURICA ROOT; TARAXACUM MONGOLICUM; LICORICE; DICTAMNUS DASYCARPUS ROOT; PUERARIA MONTANA VAR. LOBATA ROOT; ARCTIUM LAPPA FRUIT; HOUTTUYNIA CORDATA TOP; WATER; LIGUSTICUM WALLICHII ROOT; SCUTELLARIA BAICALENSIS ROOT; DENDRANTHEMA INDICUM FLOWER; SEPIA ESCULENTA BONE; DRAGON'S BLOOD

102 Rhinitis Support Cream

ACTIVE INGREDIENT

Menthol

Health Care

cooling Nasal discomfort relief

USES

According to the theory of "nasal lung coherence", the plant essence extracted from precious Chinese herbal medicine is used.This Product can help remove wind and phlegm, coordinate Yin and Yang, clear lung heat accumulation, and repair nasal mucosa.
This Product can help relieve sneezing, runny nose,Nose bleeding,dry nose, itchy eyes, acute and chronic rhinitis, Hay Fever, allergic rhinitis, sinusitis, n asa I polyps, pharyngitis, etc.

Directions

Clean the nasal cavity, apply this product evenly in the nasal cavity, gently massage to help the absorption of this product. Use 2-3 times a day.

Storage

Store in a cool dry place with lid closed tightly

When using this productAvoid contact with the eyes.

STOP USE

In case of contact with eyes, Stop use andrinse eyes thoroughly with water.

Keep out of reach of children: If accidentally ingested, get medical help orcontact a Poison Control Center immediately

Inactive ingredients

Magnolia flower, Centipeda minima whole, Xanthium fruit, Bupleurum chinense root, Angelicae Dahuricae Radix, Taraxaci Herba, Chrysanthemum indicum flower, Dictamnus dasycarpus root, Kudzu root, Arctium lappa fruit, Houttuyniae Herba, Chuanxiong Rhizoma, Scutellariae Radix, Glycyrrhizae Radix, Sepiae Endoconcha, Dragon’s blood, PETROLATUM, Water

Do not use with other ointments, sprays or liniment. People with nasal injury is prohibited to usage. If pregnant or breast-leeding: Ask a health professional before use

WARNINGS

For nasal problems only
Flammable: Kep away from excessive heat or open flame Because the nasal cavity is inflamed for a long time, In the early stage of use, there will be slight stimulation of heat, cool and numbess, Increased runny nose and sneezing, which is a normal performance and disappears with the reduction of symptoms.